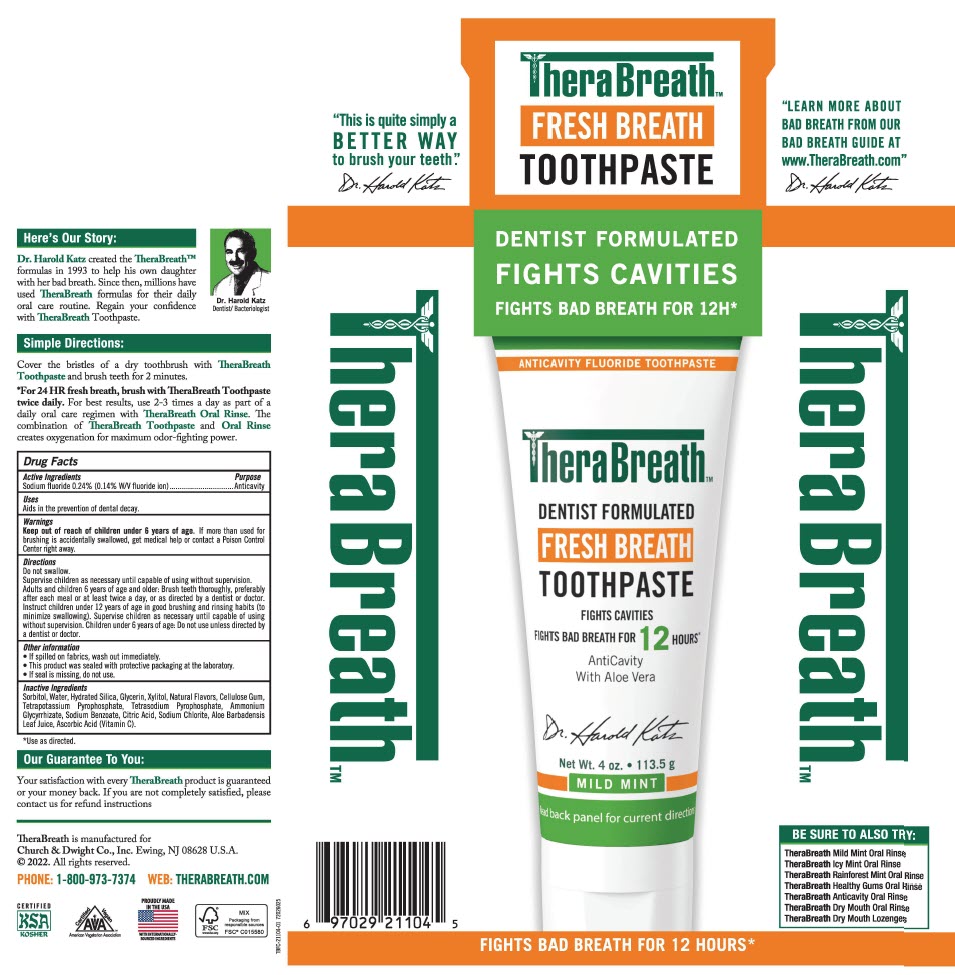 DRUG LABEL: TheraBreath Fresh Breath Anticavity Mild Mint
NDC: 10237-263 | Form: PASTE, DENTIFRICE
Manufacturer: Church & Dwight Co., Inc.
Category: otc | Type: HUMAN OTC DRUG LABEL
Date: 20240206

ACTIVE INGREDIENTS: SODIUM FLUORIDE 0.24 g/100 g
INACTIVE INGREDIENTS: WATER; SORBITOL; HYDRATED SILICA; GLYCERIN; XYLITOL; CARBOXYMETHYLCELLULOSE SODIUM, UNSPECIFIED; POTASSIUM PYROPHOSPHATE; SODIUM PYROPHOSPHATE; AMMONIUM GLYCYRRHIZATE; SODIUM BENZOATE; CITRIC ACID MONOHYDRATE; SODIUM CHLORITE; ALOE VERA LEAF; ASCORBIC ACID

TheraBreath™ Fresh Breath Toothpaste Anticavity Mild Mint

Drug Facts

Active Ingredients

Sodium fluoride 0.24% (0.14% W/V fluoride ion)

Purpose

Anticavity

Uses

Aids in the prevention of dental decay.

Warnings

Keep out of reach of children under 6 years of age. If more than used for brushing is accidentally swallowed, get medical help or contact a Poison Control Center right away.

Directions

Do not swallow.

Supervise children as necessary until capable of using without supervision.

Adults and children 6 years of age and older: Brush teeth thoroughly, preferably after each meal or at least twice a day, or as directed by a dentist or doctor. Instruct children under 12 years of age in good brushing and rinsing habits (to minimize swallowing). Supervise children as necessary until capable of using without supervision. Children under 6 years of age: Do not use unless directed by a dentist or doctor.

Other information

- If spilled on fabrics, wash out immediately.
- This product was sealed with protective packaging at the laboratory.
- If seal is missing, do not use.

Inactive Ingredients

Sorbitol, Water, Hydrated Silica, Glycerin, Xylitol, Natural Flavors, Cellulose Gum, Tetrapotassium Pyrophosphate, Tetrasodium Pyrophosphate, Ammonium Glycyrrhizate, Sodium Benzoate, Citric Acid, Sodium Chlorite, Aloe Barbadensis Leaf Juice, Ascorbic Acid (Vitamin C).

PRINCIPAL DISPLAY PANEL - 113.5 g Tube Carton

DENTIST FORMULATED
FIGHTS CAVITIES
FIGHTS BAD BREATH FOR 12H*

ANTICAVITY FLUORIDE TOOTHPASTE

TheraBreath™
DENTIST FORMULATED
FRESH BREATH
TOOTHPASTE

FIGHTS CAVITIES
FIGHTS BAD BREATH FOR 12 HOURS*

AntiCavity
With Aloe Vera

Net Wt. 4 oz. • 113.5 g

MILD MINT

Read back panel for current directions

FIGHTS BAD BREATH FOR 12 HOURS*